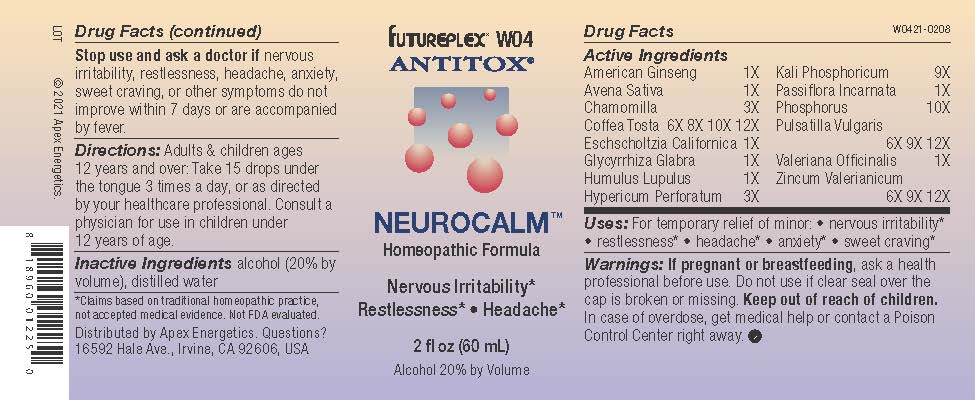 DRUG LABEL: W04
NDC: 63479-2304 | Form: SOLUTION/ DROPS
Manufacturer: Apex Energetics Inc.
Category: homeopathic | Type: HUMAN OTC DRUG LABEL
Date: 20240108

ACTIVE INGREDIENTS: HYPERICUM PERFORATUM 3 [hp_X]/1 mL; POTASSIUM PHOSPHATE, DIBASIC 9 [hp_X]/1 mL; MATRICARIA CHAMOMILLA 3 [hp_X]/1 mL; ESCHSCHOLZIA CALIFORNICA 1 [hp_X]/1 mL; PASSIFLORA INCARNATA TOP 1 [hp_X]/1 mL; VALERIAN 1 [hp_X]/1 mL; HOPS 1 [hp_X]/1 mL; PHOSPHORUS 10 [hp_X]/1 mL; PULSATILLA VULGARIS 12 [hp_X]/1 mL; ZINC VALERATE DIHYDRATE 12 [hp_X]/1 mL; AMERICAN GINSENG 1 [hp_X]/1 mL; AVENA SATIVA FLOWERING TOP 1 [hp_X]/1 mL; COFFEA ARABICA SEED, ROASTED 12 [hp_X]/1 mL; GLYCYRRHIZA GLABRA 1 [hp_X]/1 mL
INACTIVE INGREDIENTS: ALCOHOL; WATER

W04

Active Ingredients
American Ginseng | 1X
Avena Sativa | 1X
Chamomilla | 3X
Coffea Tosta | 6X 8X 10X 12X
Eschscholtzia Californica | 1X
Glycyrrhiza Glabra | 1X
Humulus Lupulus | 1X
Hypericum Perforatum | 3X
Kali Phosphoricum | 9X
Passiflora Incarnata | 1X
Phosphorus | 10X
Pulsatilla Vulgaris | 6X 9X 12X
Valeriana Officinalis | 1X
Zincum Valerianicum | 6X 9X 12X

INDICATIONS AND USAGE

Uses:

For temporary relief of minor:

nervous irritability*

restlessness*

headache*

anxiety*

sweet craving*

*Claims based on traditional homeopathic practice, not accepted medical evidence. Not FDA evaluated.

Warnings:

PREGNANCY OR BREAST FEEDING

If pregnant or breastfeeding, ask a health professional before use.

Do not use if clear seal over the cap is broken or missing.

Keep out of reach of children. In case of overdose, get medical help or contact a Poison Control Center right away.

Stop use and ask a doctor if nervous irritability, restlessness, headache, anxiety, sweet craving, or other symptoms do not improve within 7 days or are accompanied by fever.

Directions:

Adults & children ages 12 years and over: Take 15 drops under the tongue 3 times a day, or as directed by your healthcare professional. Consult a physician for use in children under 12 years of age.

Inactive Ingredients

alcohol (20% by volume), distilled water

Distributed by Apex Energetics. Questions?

16592 Hale Ave., Irvine, CA 92606, USA

PACKAGE LABEL

FUTUREPLEX® W04

ANTITOX®

NEUROCALM™

Homeopathic Formula

Nervous Irritability*

Restlessness* Headache*

2 fl oz (60 mL)

Alcohol 20% by Volume